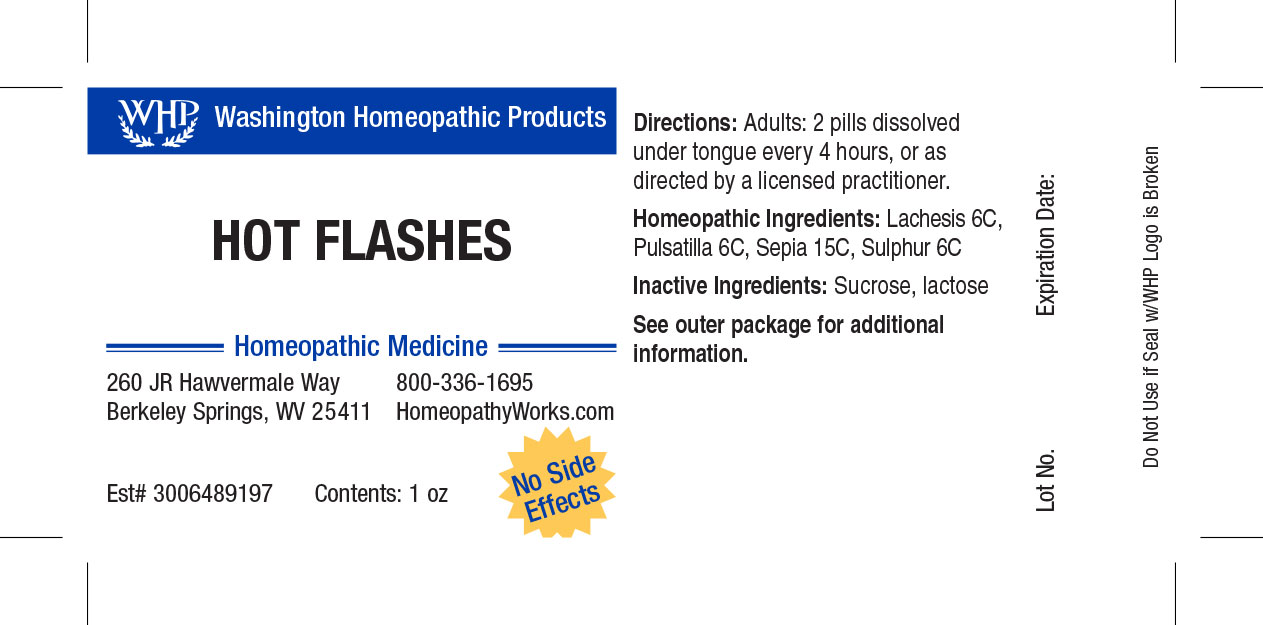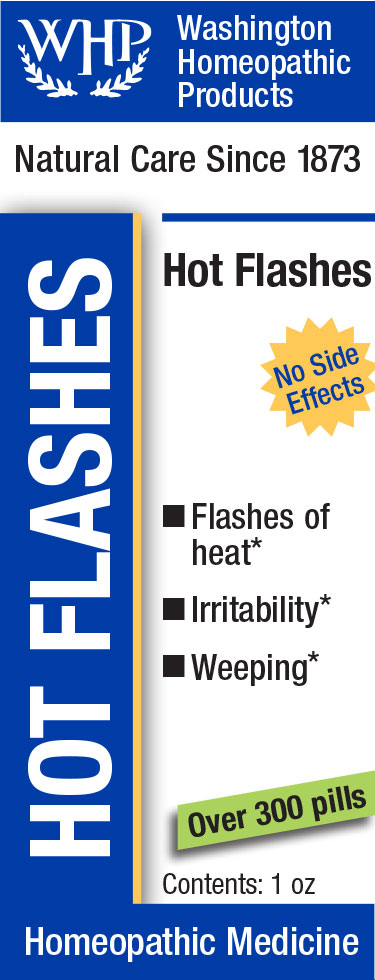 DRUG LABEL: WHP Hot Flashes
NDC: 71919-808 | Form: PELLET
Manufacturer: Washington Homeopathic Products
Category: homeopathic | Type: HUMAN OTC DRUG LABEL
Date: 20250128

ACTIVE INGREDIENTS: SULFUR 6 [hp_C]/1 1; LACHESIS MUTA VENOM 6 [hp_C]/1 1; PULSATILLA VULGARIS 6 [hp_C]/1 1; SEPIA OFFICINALIS JUICE 12 [hp_C]/1 1
INACTIVE INGREDIENTS: SUCROSE; LACTOSE

WHP Hot Flashes

ACTIVE INGREDIENTS

LACHESIS 6C

PULSATILLA 6C

SEPIA 12C

SULPHUR 6C

USES

Temporarily relieves hot flashes and other symptoms associated with change of life.

KEEP OUT OF REACH OF CHILDREN

As with all medications, keep out of reach of children.

STOP USE AND ASK DOCTOR

If symptoms persist or recur, discontinue use. If pregnant or nursing, consult a licensed practitioner before using this product.

INDICATIONS

LACHESIS Sore throat

PULSATILLA Weeping

SEPIA Indifference

SULPHUR Agitation

DIRECTIONS

Directions: Adults and children 12 years and older: 2 pills dissolved under tongue every 4 hours, or as directed by a licensed practitioner. Children 4 years to under 12 years: 1 pill dissolved under tongue every 4 hours, or as directed by a licensed practitioner. Children under 4 years: Consult a licensed practitioner.

INACTIVE INGREDIENTS

Sucrose/Lactose